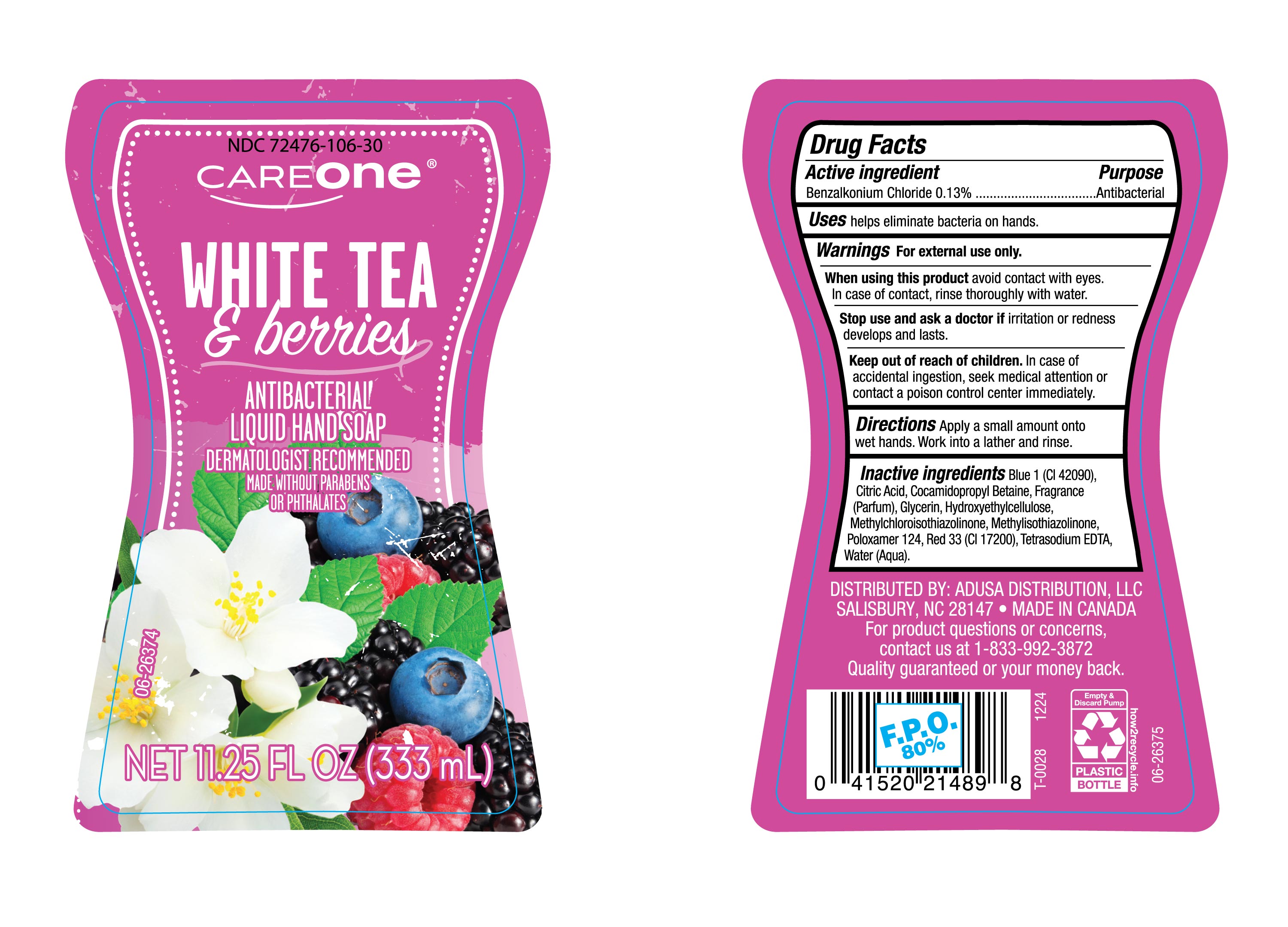 DRUG LABEL: Care One White Tea and Berry
NDC: 72476-106 | Form: LIQUID
Manufacturer: RETAIL BUSINESS SERVICES , LLC
Category: otc | Type: HUMAN OTC DRUG LABEL
Date: 20250119

ACTIVE INGREDIENTS: BENZALKONIUM CHLORIDE 130 mg/100 mL
INACTIVE INGREDIENTS: COCAMIDOPROPYL BETAINE; FRAGRANCE CLEAN ORC0600327; BLUE 1; RED 33; TETRASODIUM EDTA; HYDROXYETHYLCELLULOSE; METHYLCHLOROISOTHIAZOLINONE; WATER; CITRIC ACID; GLYCERIN; METHYLISOTHIAZOLINONE; POLOXAMER 124

NDC- 72476-106, Careone White Tea and berries.

Active Ingredient

Benzalkonium Chloride 0.13%

Purpose

Antibacterial

Uses

helps eliminate bacteria on hands.

Warnings

For external use only.

When using this product

avoid contact with eyes. In case of contact, rinse thoroughly with water.

Stop use and ask a doctor if

irritation or redness develops and lasts.

Keep out of reach of children.

In case of accidental ingestion, seek medical attention or contact a poison control center immediately.

Directions

Apply a small amount onto wet hands. Work into a lather and rinse.

Inactive Ingredients

Blue 1 (CI 42090), Citric Acid, Cocamidopropyl Betaine, Fragrance (Parfum), Glycerin, Hydroxyethylcellulose, Methylchloroisothiazolinone, Methylisothiazolinone, Poloxamer 124, Red 33 (CI 17200), Tetrasodium EDTA, Water (Aqua).